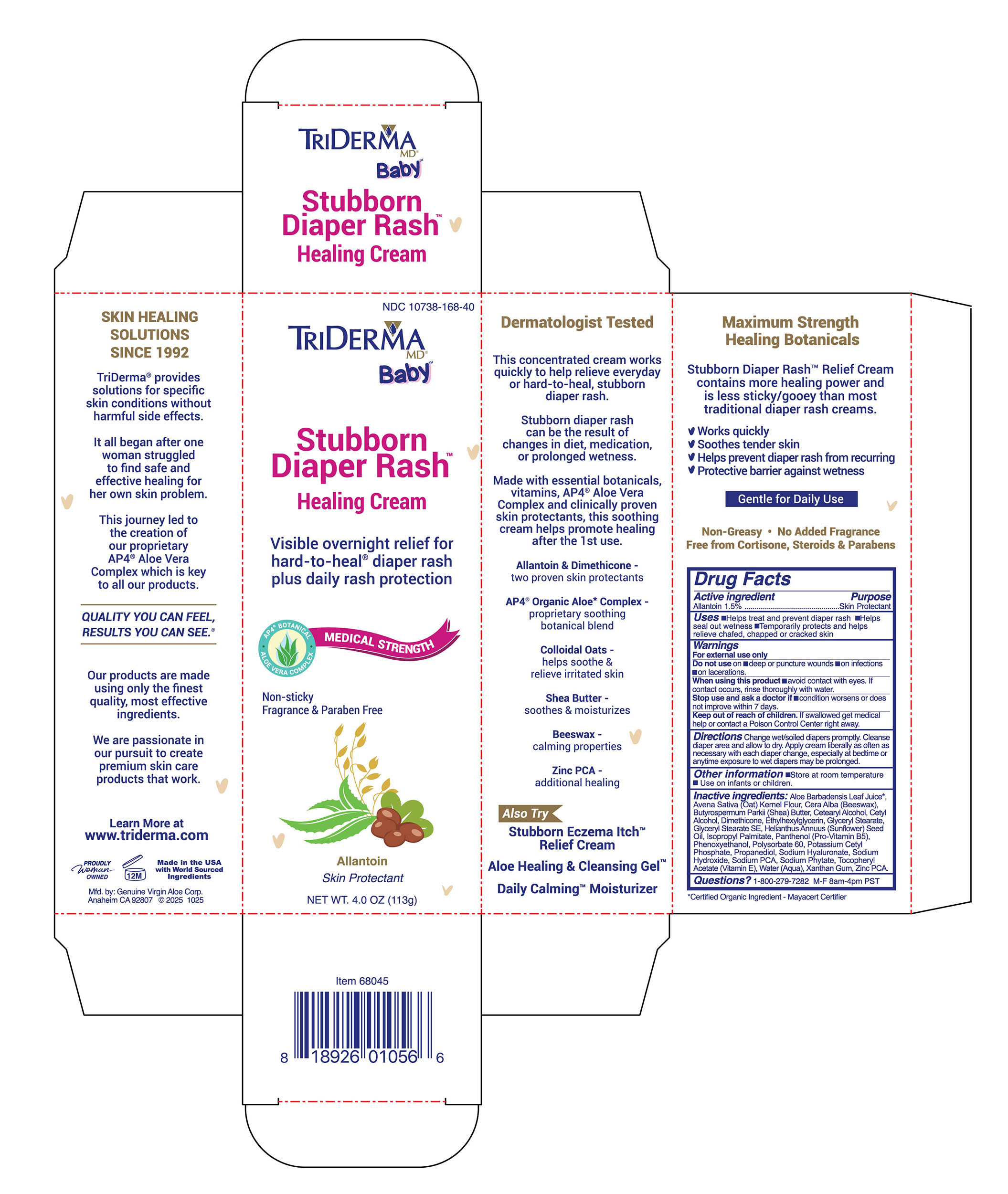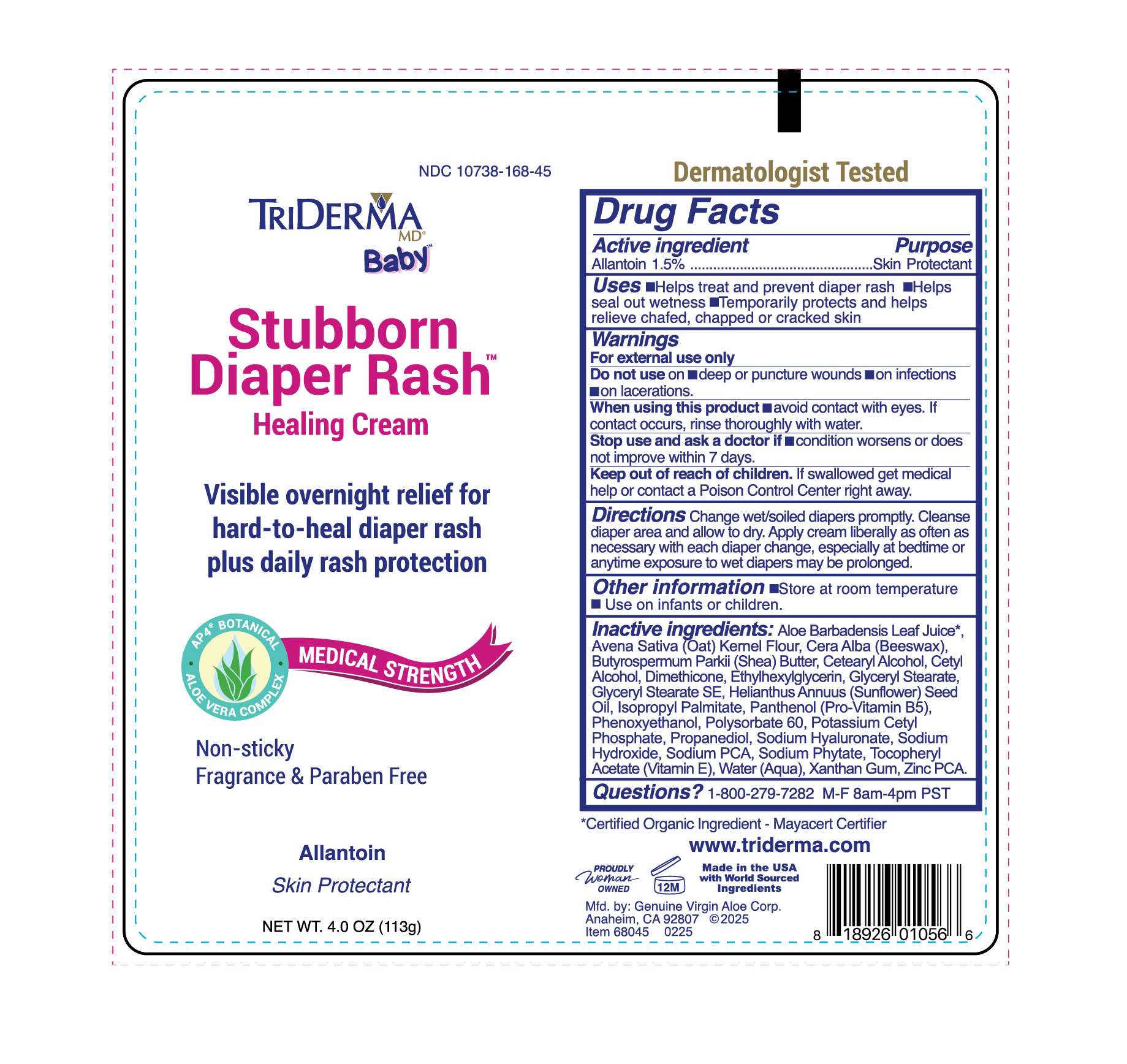 DRUG LABEL: TriDerma Stubborn Diaper Rash Relief
NDC: 10738-168 | Form: CREAM
Manufacturer: Genuine Virgin Aloe Corporation
Category: otc | Type: HUMAN OTC DRUG LABEL
Date: 20260128

ACTIVE INGREDIENTS: ALLANTOIN 1.5 g/100 g
INACTIVE INGREDIENTS: SUNFLOWER OIL; SODIUM PCA; ALOE VERA LEAF JUICE; SODIUM PHYTATE; BEESWAX; CETYL ALCOHOL; PANTHENOL; GLYCERYL STEARATE; ISOPROPYL PALMITATE; POTASSIUM CETYL PHOSPHATE; CETEARYL ALCOHOL; GLYCERYL STEARATE SE; AVENA SATIVA (OAT) STARCH; ETHYLHEXYLGLYCERIN; WATER; SHEA BUTTER; DIMETHICONE 100; POLYSORBATE 60; PROPANEDIOL; ZINC PCA; .ALPHA.-TOCOPHEROL ACETATE; PHENOXYETHANOL; SODIUM HYALURONATE; XANTHAN GUM; SODIUM HYDROXIDE

TriDerma Stubborn Diaper Rash Cream

Active Ingredient

Allantoin 1.5%

Purpose

Skin Protectant

INDICATIONS AND USAGE

- Helps treat and prevent diaper rash
- Helps seal out wetness
- Temporarily protects and helps relieve chafed, chapped or cracked skin

WARNINGS

For external use only

Do not use on

- deep or puncture wounds
- on infections
- on lacerations

WHEN USING

avoid contact with eyes. If contact occurs, rinse thoroughly with water.

STOP USE

if condition worsens or does not improve within 7 days

KEEP OUT OF REACH OF CHILDREN

if swallowed get medical help or contact a Poison Control Center right away.

QUESTIONS

Questions: 1-800-279-7282 M-F 8 am-4pm PST

STORAGE AND HANDLING

- Store at room temperature
- for use on infants or children

INACTIVE INGREDIENT

Aloe Barbadensis Leaf Juice*,
Avena Sativa (Oat) Kernel Flour, Cera Alba (Beeswax),
Butyrospermum Parkii (Shea) Butter, Cetearyl Alcohol, Cetyl
Alcohol, Dimethicone, Ethylhexylglycerin, Glyceryl Stearate,
Glyceryl Stearate SE, Helianthus Annuus (Sunflower) Seed
Oil, Isopropyl Palmitate, Panthenol (Pro-Vitamin B5),
Phenoxyethanol, Polysorbate 60, Potassium Cetyl
Phosphate, Propanediol, Sodium Hyaluronate, Sodium
Hydroxide, Sodium PCA, Sodium Phytate, Tocopheryl
Acetate (Vitamin E), Water (Aqua), Xanthan Gum, Zinc PCA.

DOSAGE AND ADMINISTRATION

Change wet/soiled diapers promptly. Cleanse diaper area and allow to dry. Apply cream liberally as often as necessary with each diaper change, especially at bedtime or anytime exposure to wet diapers may be prolonged.